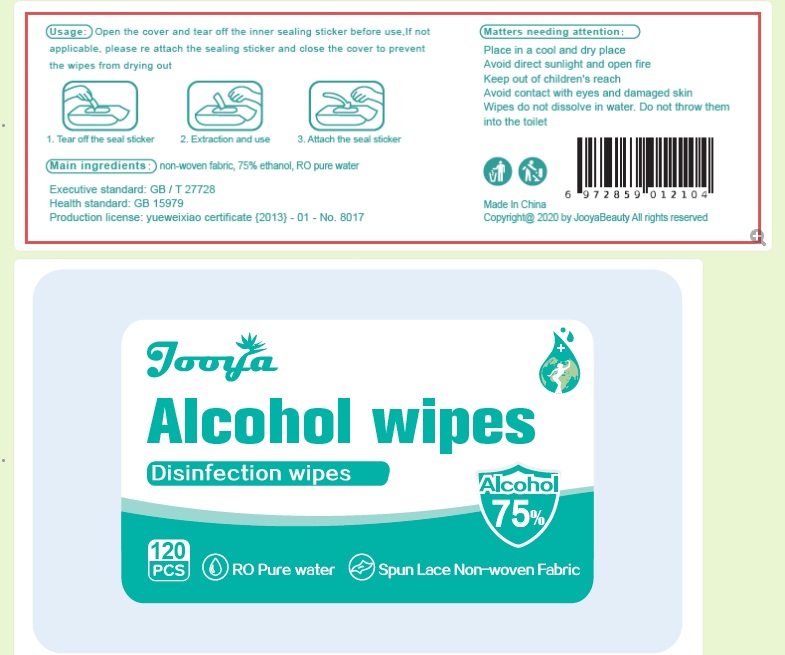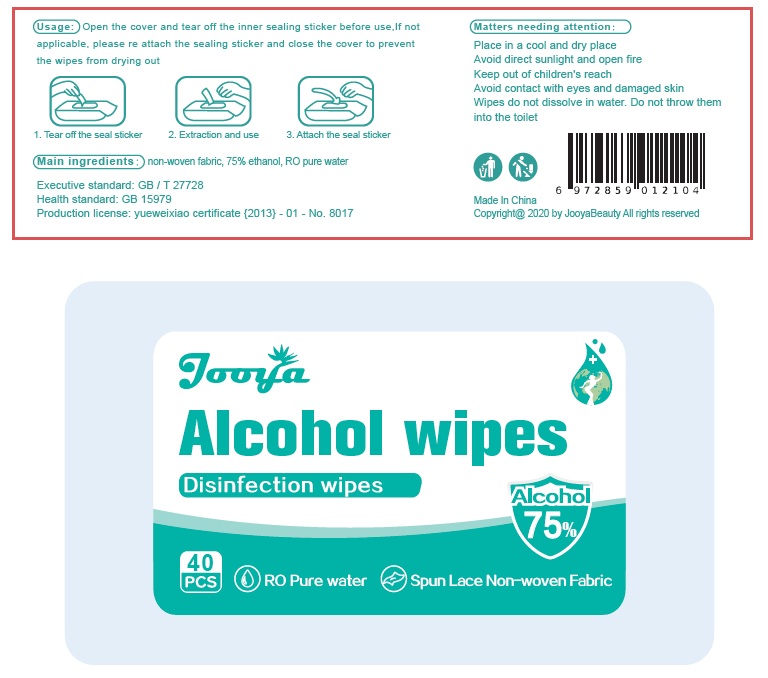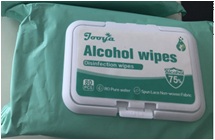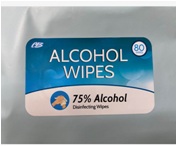 DRUG LABEL: ALCOHOL Wipe
NDC: 75715-201 | Form: CLOTH
Manufacturer: Shenzhen Itsuwa Technology Co., Ltd.
Category: otc | Type: HUMAN OTC DRUG LABEL
Date: 20200511

ACTIVE INGREDIENTS: ALCOHOL 1 mL/1 1
INACTIVE INGREDIENTS: GLYCERIN; WATER

ALCOHOL Wipe

ALCOHOL Wipe

Active Ingredient(s)

Alcohol 1mL/pcs. Purpose: Antiseptic

Purpose

Antiseptic

Use

ALCOHOL Wipe to help reduce bacteria that potentially can cause disease. For use when soap and water are not available.

Warnings

For external use only. Flammable. Keep away from heat or flame

Do not use

- in children less than 2 months of age
- on open skin wounds

When using this product keep out of eyes, ears, and mouth. In case of contact with eyes, rinse eyes thoroughly with water.
Stop use and ask a doctor if irritation or rash occurs. These may be signs of a serious condition.
Keep out of reach of children. If swallowed, get medical help or contact a Poison Control Center right away.

Stop use and ask a doctor if irritation or rash occurs. These may be signs of a serious condition.

Keep out of reach of children. If swallowed, get medical help or contact a Poison Control Center right away.

Directions

- 1,Tear off the seal sticker. 2, Extraction and use. 3, Attach the seal sticker
- Supervise children under 6 years of age when using this product to avoid swallowing.

Other information

- Store between 15-30C (59-86F)
- Avoid freezing and excessive heat above 40C (104F)

Inactive ingredients

glycerin, purified water USP